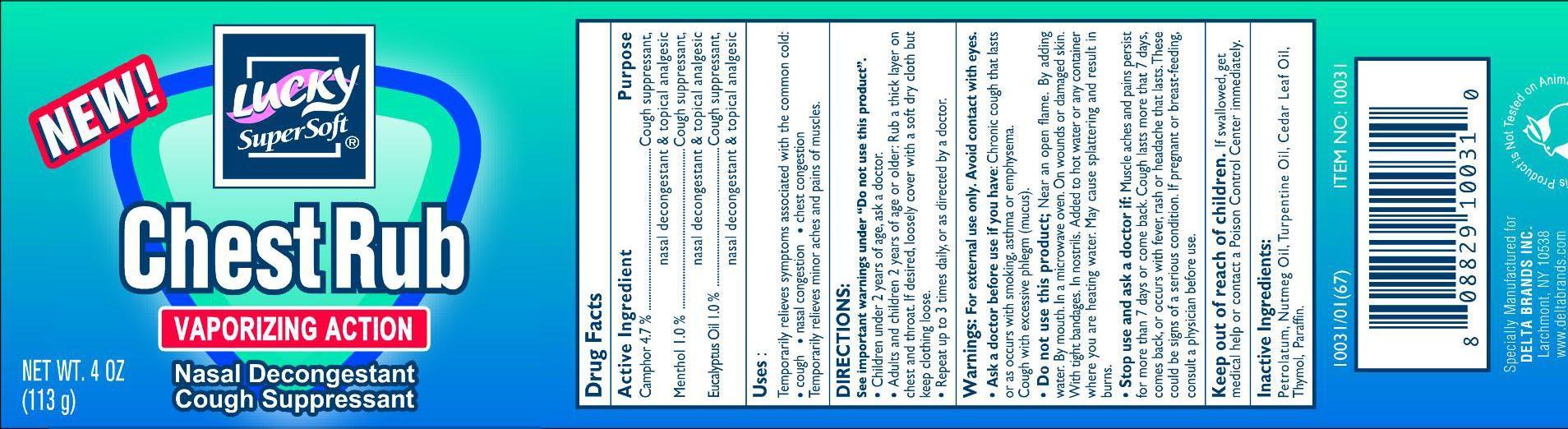 DRUG LABEL: Chestrub
NDC: 20276-100 | Form: OINTMENT
Manufacturer: Delta Brands Inc
Category: otc | Type: HUMAN OTC DRUG LABEL
Date: 20241217

ACTIVE INGREDIENTS: CAMPHOR (SYNTHETIC) 4.7 g/100 g; MENTHOL 1 g/100 g; EUCALYPTUS OIL 1 g/100 g
INACTIVE INGREDIENTS: CEDAR LEAF OIL; NUTMEG; PARAFFIN; PETROLATUM; THYMOL; TURPENTINE

Active Ingredients

Camphor 4.7%

Menthol 1.0%

Eucalyptus Oil 1.0%

Purpose

Cough Suppressant

Nasal Decongestant

Topical Anlagesic

Uses

Temporarily relieves symptoms associated with the common cold:

- cough
- nasal congestion
- chest congestion

Temporarily relieves minor aches and pains of muscles

Directions

See important warnings under "Do not Use this product"

- Children under 2 years of age, ask a doctor
- Adults and children 2 years of age and older: rub a thick layer on chest and throat. If desired loosely cover with a soft cloth but keep clothing loose.
- Repeat up to 3 times daily, or as directed by a doctor

Warnings

For external use only. Avoid contact with eyes.

Ask a doctor before use if you have

Chronic cough that lasts or occurs with smoking, asthma or emphysema.

Cough with excessive phlegm (mucus).

Do not use this product

Near an open flame. By adding water. By mouth. In a microwave oven. On wounds or damaged skin. With tight bandages. In nostrils. added to hot water or any container where you are heating water. May cause splattering and result in burns.

Stop use and ask a doctor

if Muscle aches and pains persist for more than 7 days comes back, or occurs with fever, rash or headache that lasts.

These could be signs of a serious condition. If pregnant or breast-feeding consult a physician before use.

Keep out of reach of children

If swallowed get medical help or contact a Poison Control Center immediately.

Inactive Ingredients

Petrolatum, Nutmeg Oil, Turpentine Oil, Cedar Leaf Oil, Thymol, Paraffin